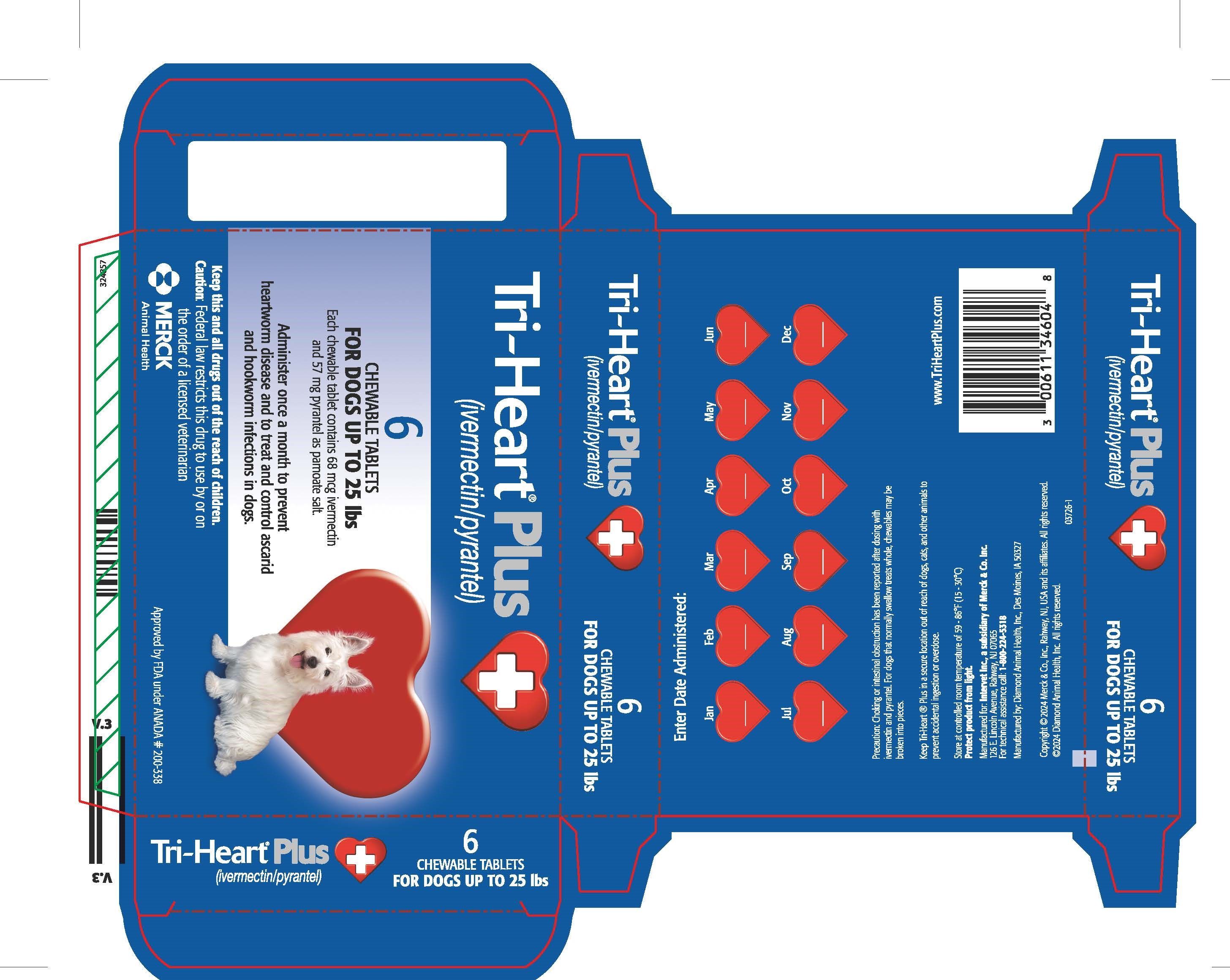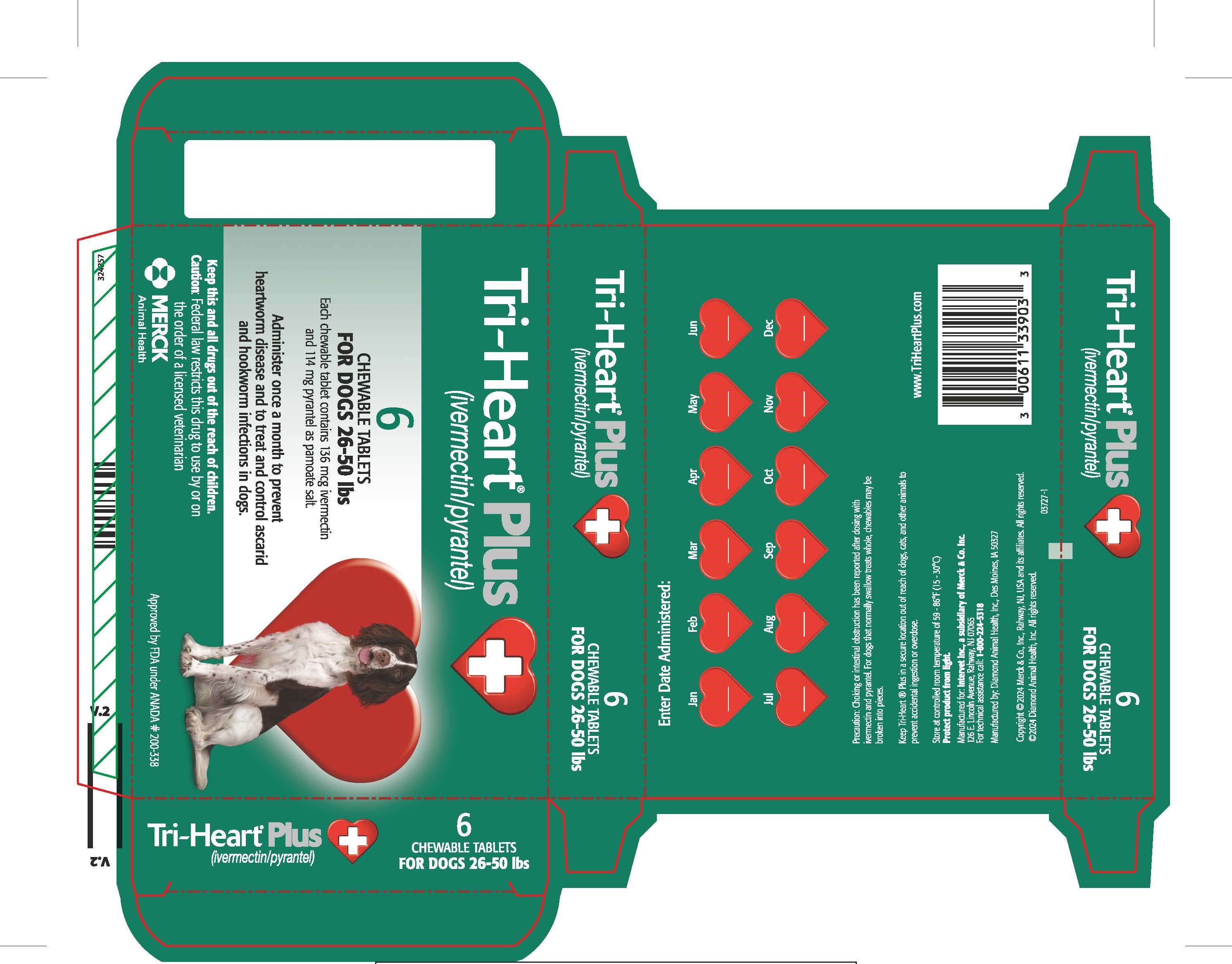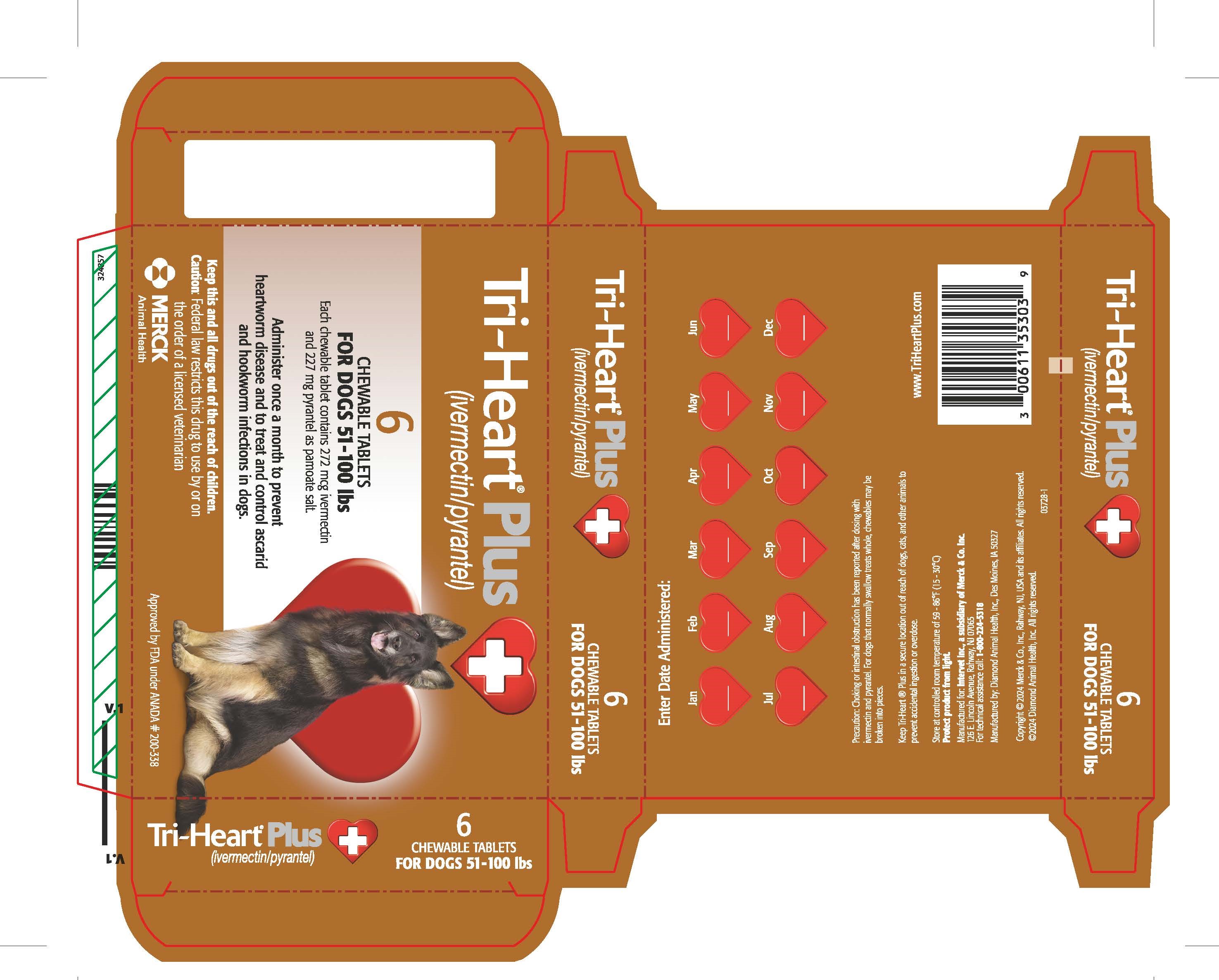 DRUG LABEL: Tri-Heart Plus
NDC: 0061-1346 | Form: TABLET, CHEWABLE
Manufacturer: Intervet, Inc. a subsidiary of Merck and Company, Inc.
Category: animal | Type: PRESCRIPTION ANIMAL DRUG LABEL
Date: 20260129

ACTIVE INGREDIENTS: IVERMECTIN 68 ug/1 1; PYRANTEL PAMOATE 57 mg/1 1

Tri-Heart Plus (Ivermectin and Pyrantel)

Package Insert Top

Tri-Heart® Plus
(ivermectin/pyrantel)
Chewable Tablets

Caution: Federal law restricts this drug to use by or on the order of a licensed veterinarian.

VETERINARY INDICATIONS

INDICATIONS: For use in dogs to prevent canine heartworm disease by eliminating the tissue stage of heartworm larvae (Dirofilaria immitis) for a month (30 days) after infection and for the treatment and control of roundworms (Toxocara canis, Toxascaris leonina) and hookworms (Ancylostoma caninum, Uncinaria stenocephala, Ancylostoma braziliense).

DOSAGE AND ADMINISTRATION

DOSAGE: Tri-Heart® Plus should be administered orally at monthly intervals at the
recommended minimum dose level of 6 mcg of ivermectin per kilogram (2.72 mcg/lb) and 5 mg of pyrantel (as
pamoate salt) per kg (2.27 mg/lb) of body weight. The recommended dosing schedule for prevention of canine
heartworm disease and for the treatment and control of roundworms and hookworms is as follows:

Dog Weight | Chewable Tablets per Month | Ivermectin Content | Pyrantel Content | Color Coding on Blister Card and Carton
Up to 25 lbs. | 1 | 68 mcg | 57 mg | Blue
26 to 50 lbs. | 1 | 136 mcg | 114 mg | Green
51 to 100 lbs. | 1 | 272 mcg | 227 mg | Brown

Tri-Heart® Plus is recommended for dogs 6 weeks of
age and older. For dogs over 100 lbs, use the appropriate combination of these tablets.
ADMINISTRATION: Remove only one chewable tablet at a time from the blister card.
Because most dogs find Tri-Heart® Plus palatable, the product can be
offered to the dog by hand. Alternatively, it may be added intact to a small amount of dry food
or placed in the back of the dog’s mouth for forced swallowing.
Care should be taken that the dog consumes the complete dose, and treated animals should
be observed for a few minutes after administration to ensure that part of the dose is not lost
or rejected. If it is suspected that any of the dose has been lost, redosing is recommended.
Tri-Heart® Plus should be given at monthly intervals during the period of the
year when mosquitoes (vectors), potentially carrying infective heartworm larvae, are active.
The initial dose must be given within a month (30 days) after the dog’s first exposure to mosquitoes.
The final dose must be given within a month (30 days) after the dog’s last exposure
to mosquitoes.
When replacing another heartworm preventive product in a heartworm disease preventive
program, the first dose of Tri-Heart® Plus must be given within a month (30
days) of the last dose of the former medication.
If the interval between doses exceeds a month (30 days), the efficacy of ivermectin can be
reduced. Therefore, for optimal performance, the chewable tablet must be given once a
month on or about the same day of the month. If treatment is delayed, whether by a few days
or many, immediate treatment with Tri-Heart® Plus and resumption of the
recommended dosing regimen minimizes the opportunity for the development of adult
heartworms.
Monthly treatment with Tri-Heart® Plus also provides effective treatment
and control of roundworms (T. canis, T. leonina) and hookworms (A. caninum, U. stenocephala,
A. braziliense). Clients should be advised of measures to be taken to prevent reinfection with
intestinal parasites.

EFFICACY: Tri-Heart® Plus (ivermectin/pyrantel) chewable tablets given orally using the recommended dose and
regimen, are effective against the tissue larval stage of D. immitis for a month (30 days)
after infection and, as a result, prevent the development of the adult stage. Tri-Heart®
Plus chewable tablets are also effective against canine roundworms (T. canis, T. leonina)
and hookworms (A. caninum, U. stenocephala, A. braziliense).
ACCEPTABILITY: In acceptability trials, Tri-Heart® Plus is shown to be
a palatable oral dosage form that was consumed at first offering by the majority of dogs.

PRECAUTIONS

PRECAUTIONS: All dogs should be tested for existing heartworm infection before starting
treatment with Tri-Heart® Plus which is not effective against adult
D. immitis. Infected dogs must be treated to remove adult heartworms and microfilariae
before initiating a program with Tri-Heart® Plus.
While some microfilariae may be killed by the ivermectin in Tri-Heart® Plus
at the recommended dose level, Tri-Heart® Plus is not effective
for microfilariae clearance. A mild hypersensitivity-type reaction, presumably due to
dead or dying microfilariae and particularly involving a transient diarrhea has been
observed in clinical trials with ivermectin alone after treatment of some dogs that have
circulating microfilariae.

Choking or intestinal obstruction has been reported after dosing with ivermectin/pyrantel. For dogs that normally swallow treats whole, chewables may be broken into pieces (see Post-Approval Experience).

Keep this and all drugs out of the reach of children. In case of ingestion by humans, clients
should be advised to consult a physician immediately. Physicians may contact a Poison Control Center for
advice concerning cases of ingestion by humans.

Keep Tri-Heart Plus in a secure location out of reach of dogs, cats, and other animals to prevent accidental ingestion or overdose.

Store at controlled room temperature of 59-86o F (15-30o C). Protect product from light.

ADVERSE REACTIONS

ADVERSE REACTIONS: In clinical field trials with ivermectin/pyrantel, vomiting or diarrhea
within 24 hours of dosing was observed (1.1% of administered doses).

POST-APPROVAL EXPERIENCE: The following adverse events are based on post-approval adverse
drug experience reporting for ivermectin/pyrantel. Not all adverse events are reported to FDA/CVM.
It is not always possible to reliably estimate the adverse event frequency or establish a causal
relationship to product exposure using these data.

The following adverse events reported in dogs are listed in decreasing order of reporting frequency:
Vomiting, diarrhea, lethargy, anorexia, seizures, ataxia, muscle tremors, hypersalivation, pruritus.

In some cases, choking or intestinal obstruction has been reported after administration of
ivermectin/pyrantel.

Contact Information: Contact Merck Animal Health at 1-800-224-5318 or www.TriHeartPlus.com.
To report suspected adverse drug experiences, contact Merck Animal Health at 1-800-224-5318.
For additional information about reporting adverse drug experiences for animal drugs, contact FDA
at 1-888-FDA-VETS or http://www.fda.gov/reportanimalae To obtain a Safety Data Sheet(s), contact
Merck Animal Health at 1-800-224-5318 or www.Tri-HeartPlus.com.

SUMMARY OF SAFETY AND EFFECTIVENESS

SAFETY: Studies with ivermectin indicate that certain dogs of the Collie breed are more
sensitive to the effects of ivermectin administered at elevated dose levels (more than 16
times the target use level of 6 mcg/kg) than dogs of other breeds. At elevated doses,
sensitive dogs showed adverse reactions which included mydriasis, depression, ataxia,
tremors, drooling, paresis, recumbency, excitability, stupor, coma and death. Ivermectin
demonstrated no signs of toxicity at 10 times the recommended dose (60 mcg/kg) in sensitive
Collies. Results of these trials and bioequivalency studies support the safety of
ivermectin products in dogs, including Collies, when used as recommended.
Ivermectin/pyrantel has shown a wide margin of safety at the recommended dose level in
dogs, including pregnant or breeding bitches, stud dogs and puppies aged 6 or more
weeks. In clinical trials, many commonly used flea collars, dips, shampoos,
anthelmintics, antibiotics, vaccines and steroid preparations have been administered
with ivermectin/pyrantel in a heartworm disease preventive program.
In one trial, where some pups had parvovirus, there was a marginal reduction in efficacy
against intestinal nematodes, possibly due to a change in intestinal transit time.

HOW SUPPLIED

HOW SUPPLIED: Tri-Heart® Plus is available in three dosage strengths (See
DOSAGE section) for dogs of different weights. Each strength comes in convenient packs of 6
chewable tablets.
Manufactured for: Intervet Inc. a subsidiary of Merck & Co. Inc., 126 E. Lincoln Avenue, Rahway, NJ 07065
Manufactured by: Diamond Animal Health, Inc., Des Moines, IA 50327
©2024 Diamond Animal Health. All rights reserved.
02356
Approved by FDA under ANADA # 200-338
www.TriHeartPlus.com

PACKAGE LABEL

25 lb unit carton

PACKAGE LABEL

26-50 lb unit carton

PACKAGE LABEL

51-100 lb unit carton